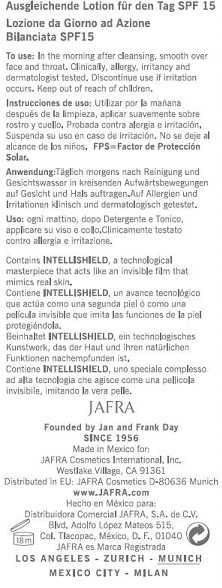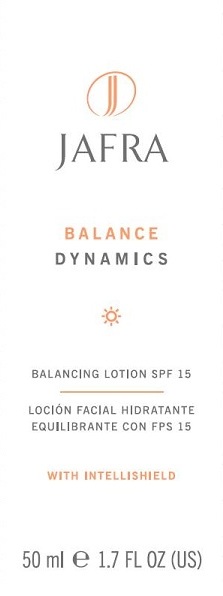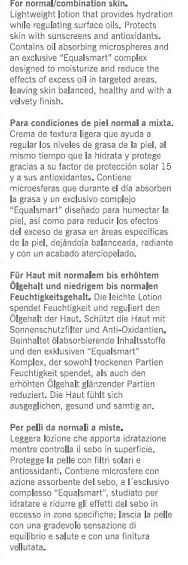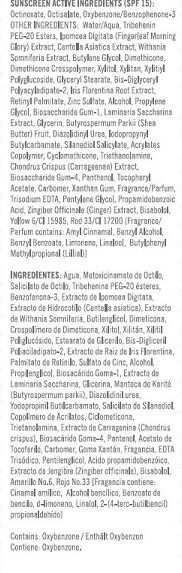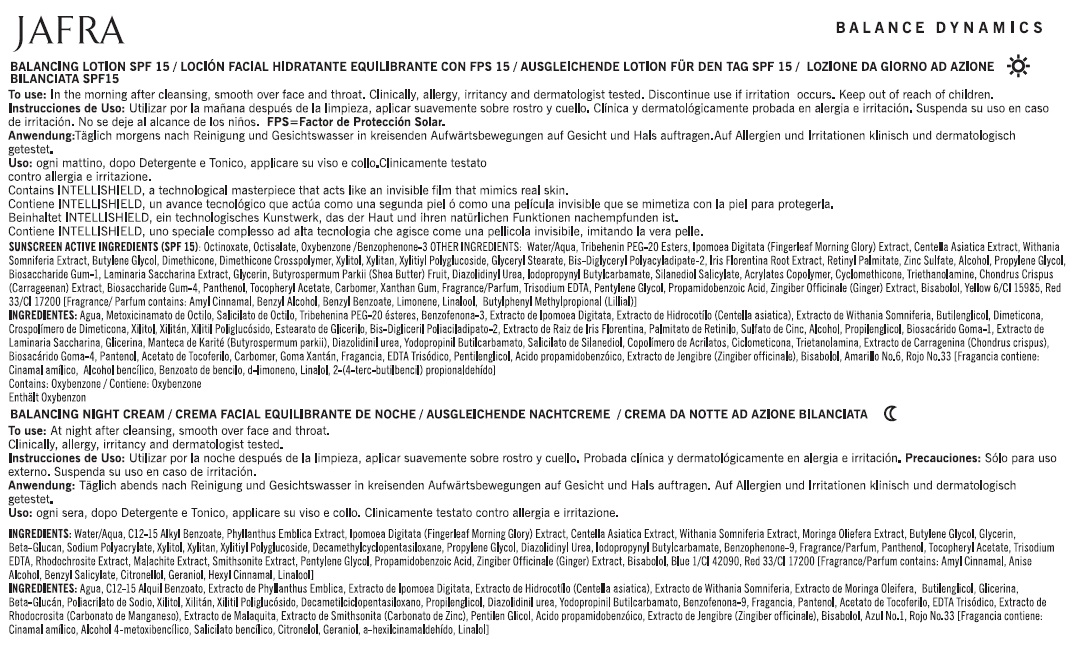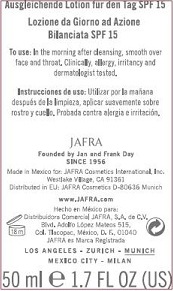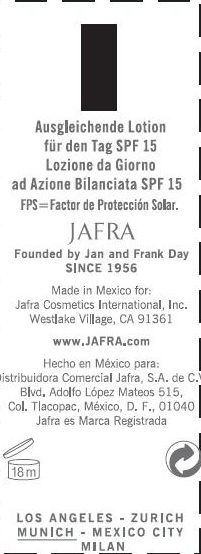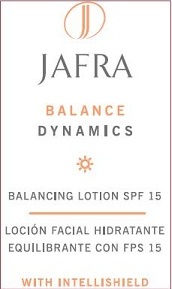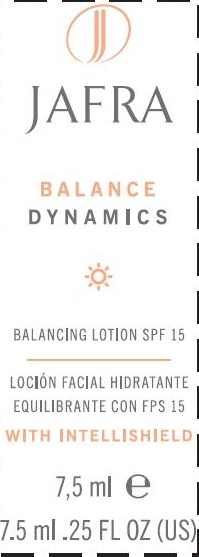 DRUG LABEL: BALANCE DYNAMICS BALANCING
NDC: 68828-150 | Form: LOTION
Manufacturer: JAFRA COSMETICS INTERNATIONAL
Category: otc | Type: HUMAN OTC DRUG LABEL
Date: 20120531

ACTIVE INGREDIENTS: OCTISALATE 4 g/100 mL; OXYBENZONE 2 g/100 mL; OCTINOXATE 7 g/100 mL
INACTIVE INGREDIENTS: WATER; TRIBEHENIN PEG-20 ESTERS; IPOMOEA MAURITIANA TUBER; CENTELLA ASIATICA LEAF; WITHANIA SOMNIFERA FLOWER; BUTYLENE GLYCOL; DIMETHICONE; XYLITOL; XYLITYLGLUCOSIDE; GLYCERYL MONOSTEARATE; DIGLYCERIN; IRIS GERMANICA VAR. FLORENTINA ROOT; VITAMIN A PALMITATE; ZINC SULFATE; ALCOHOL; PROPYLENE GLYCOL; BIOSACCHARIDE GUM-1; SACCHARINA LATISSIMA THALLUS; SHEA BUTTER; DIAZOLIDINYL UREA; IODOPROPYNYL BUTYLCARBAMATE; SILANETRIOL; CARBOMER COPOLYMER TYPE A (ALLYL PENTAERYTHRITOL CROSSLINKED); CYCLOMETHICONE; TROLAMINE; CHONDRUS CRISPUS; PANTHENOL; .ALPHA.-TOCOPHEROL ACETATE; CARBOMER HOMOPOLYMER (ALLYL SUCROSE CROSSLINKED); XANTHAN GUM; EDETATE TRISODIUM; PENTYLENE GLYCOL; BENZOIC ACID; GINGER; LEVOMENOL; FD&C YELLOW NO. 6; D&C RED NO. 33

BALANCE DYNAMICS BALANCING LOTION SPF-15

SUNSCREEN ACTIVE INGREDIENT (SPF 15):
OCTINOXATE, OCTISALATE, OXYBENZONE/BENZOPHENONE-3

PURPOSE: SUNSCREEN

INACTIVE INGREDIENT

OTHER INGREDIENTS: WATER/AQUA, TRIBEHENIN PEG-20 ESTERS, IPOMOEA DIGITATA (FINGERLEAF MORNING GLORY) EXTRACT, CENTELLA ASIATICA EXTRACT, WITHANIA SOMNIFERIA EXTRACT, BUTYLENE GLYCOL, DIMETHICONE, DIMETHICONE CROSSPOLYMER, XYLITOL, XYLITAN, XYLITYL POLYGLUCOSIDE, GLYCERYL STEARATE, BIS-DIGLYCERYL POLYACRYLADIPATE-2, IRIS FLORENTINA ROOT EXTRACT, RETINYL PALMITATE, ZINC SULFATE, ALCOHOL, PROPYLENE GLYCOL, BIOSACCHARIDE GUM-1, LAMINARIA SACCHARINA EXTRACT, GLYCERIN, BUTYROSPERMUM PARKII (SHEA BUTTER) FRUIT, DIAZOLIDINYL UREA, IODOPROPYNYL BUTYLCARBAMATE, SILANEDIOL SALICYLATE, ACRYLATES COPOLYMER, CYCLOMETHICONE, TRIETHANOLAMINE, CHONDRUS CRISPUS (CARRAGEENAN) EXTRACT, BIOSACCHARIDE GUM-4, PANTHENOL, TOCOPHERYL ACETATE, CARBOMER, XANTHAN GUM, FRAGRANCE/PARFUM, TRISODIUM EDTA, PENTYLENE GLYCOL, PROPAMIDOBENZOIC ACID, ZINGIBER OFFICINALE (GINGER) EXTRACT, BISABOLOL, YELLOW 6/CI 15985, RED 33/CI 17200 [FRAGRANCE/PARFUM CONTAINS: AMYL CINNAMAL, BENZYL ALCOHOL, BENZYL BENZOATE, LIMONENE, LINALOOL, BUTYLCHEMYL METHYLPROPIONAL (LILLIAL)].

INDICATIONS AND USAGE

BALANCING LOTION SPF 15

DOSAGE AND ADMINISTRATION

TO USE: IN THE MORNING AFTER CLEANSING, SMOOTH OVER FACE AND THROAT.

WARNINGS

DISCONTINUE USE IF IRRITATION OCCURS.

KEEP OUT OF REACH OF CHILDREN.

PACKAGE LABEL

JAFRA

BALANCE

DYNAMICS

BALANCING LOTION SPF 15